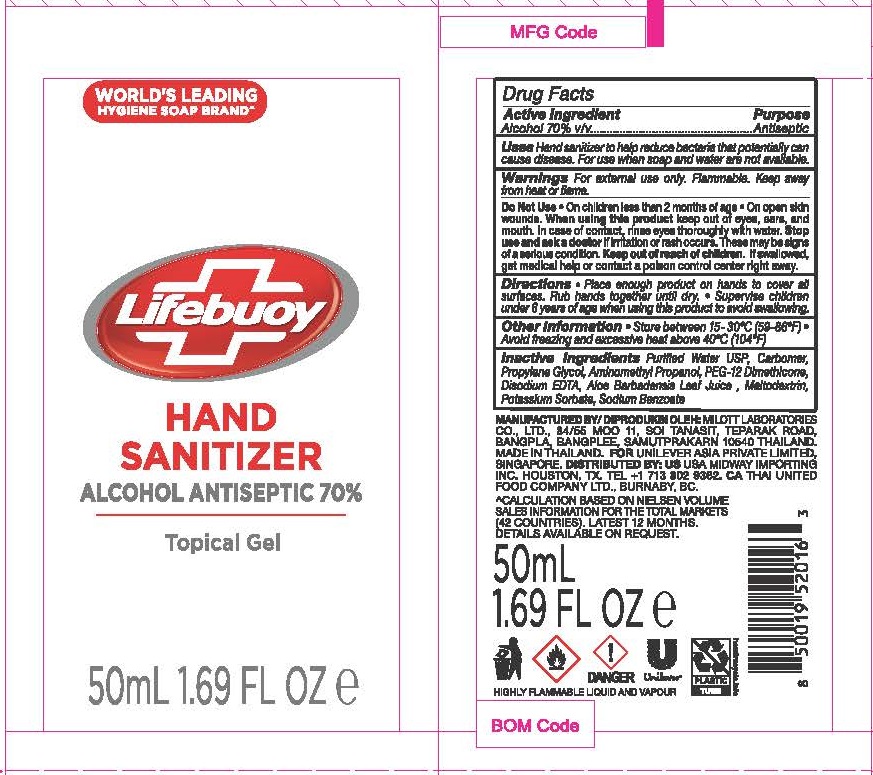 DRUG LABEL: Lifebuoy Hand Sanitizer
NDC: 50069-107 | Form: GEL
Manufacturer: UNILEVER ASIA PRIVATE LIMITED
Category: otc | Type: HUMAN OTC DRUG LABEL
Date: 20200622

ACTIVE INGREDIENTS: ALCOHOL 70 mL/100 mL
INACTIVE INGREDIENTS: WATER; CARBOMER HOMOPOLYMER, UNSPECIFIED TYPE; PROPYLENE GLYCOL; AMINOMETHYLPROPANOL; PEG-12 DIMETHICONE; EDETATE DISODIUM; ALOE VERA LEAF; MALTODEXTRIN; POTASSIUM SORBATE; SODIUM BENZOATE

Lifebuoy Hand Sanitizer - 70% Alcohol

ACTIVE INGREDIENT

Alcohol 70% v/v

PURPOSE

ANTISEPTIC

USE

Hand sanitizer to help reduce bacteria that potentially can cause disease. For use when soap and water are not available.

WARNINGS

For external use only. Flammable. Keep away from heat or flame.

Do Not Use

- On children less than 2 months of age
- On open skin wounds.

When using this product keep out of eyes, ears, and mouth. In case of contact, rinse eyes thoroughly with water.

Stop use and ask a doctor if irritation or rash occurs. These may be signs of a serious condition.

Keep out of reach of children.

If swallowed, get medical help or contact a Poison Control Center right away.

Keep out of reach of children. If swallowed, get medical help or contact a poison control center right away.

DIRECTIONS

- Place enough product on hands to cover all surfaces. Rub hands together until dry
- Supervise children under 6 years of age when using this product to avoid swallowing.

INACTIVE INGREDIENTS

Purified Water USP, Carbomer, Propylene Glycol, Aminomethyl Propanol, PEG-12 Dimethicone, Disodium EDTA, Aloe Barbadensis Extract, Maltodextrin, Potassium Sorbate, Sodium Benzoate

OTHER INFORMATION

- Store between 15-30℃ (59-86℉)
- Avoid freezing and excessive heat above 40℃ (104℉)